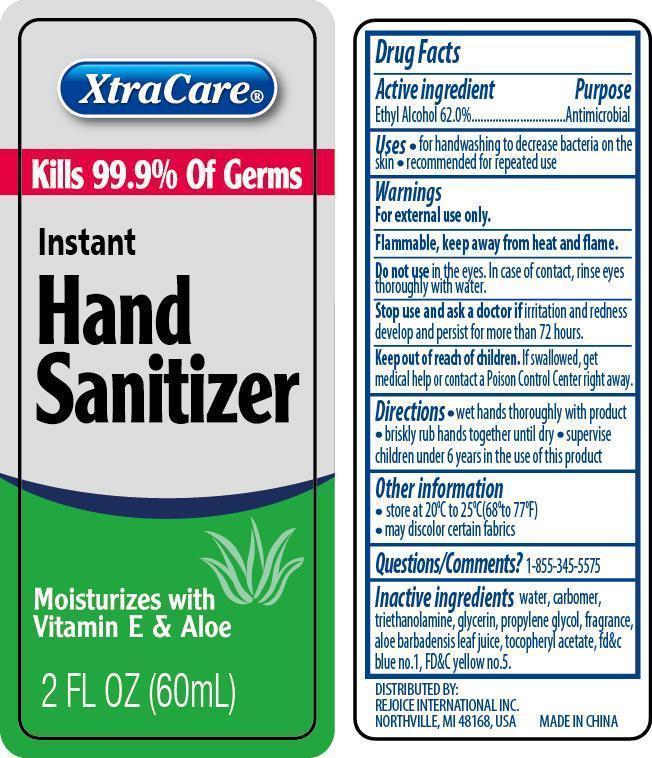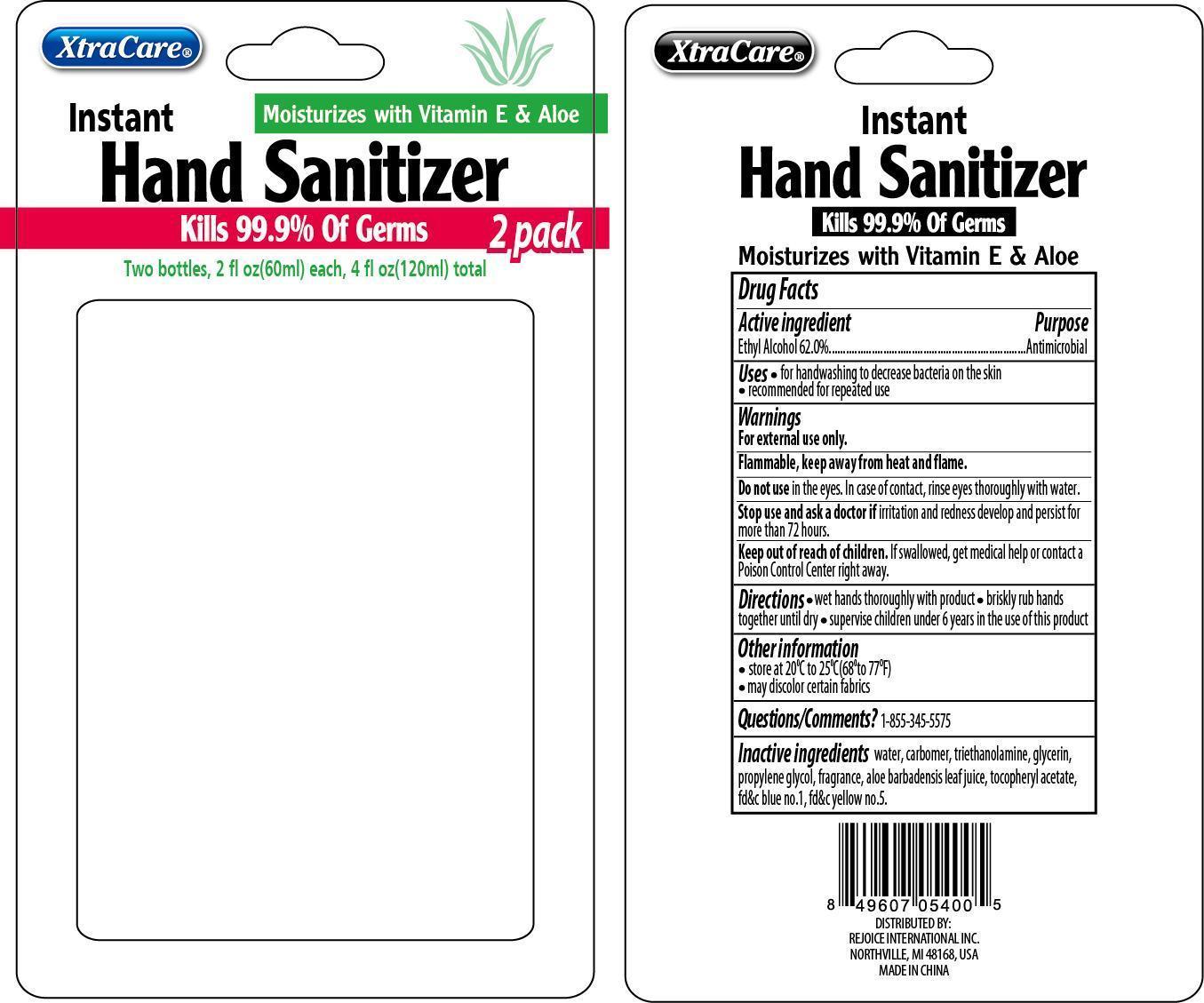 DRUG LABEL: XtraCare Instant Hand Sanitizer
NDC: 57337-059 | Form: LIQUID
Manufacturer: Rejoice International
Category: otc | Type: HUMAN OTC DRUG LABEL
Date: 20240228

ACTIVE INGREDIENTS: ALCOHOL 37 g/60 g
INACTIVE INGREDIENTS: WATER; CARBOMER COPOLYMER TYPE A (ALLYL PENTAERYTHRITOL CROSSLINKED); TROLAMINE; GLYCERIN; PROPYLENE GLYCOL; TOCOPHEROL

XtraCare Instant Hand Sanitizer

Active Ingredient Purpose

Ethyl Alcohol 62.0% ...................... Antimicrobial

Uses

for handwashing to decrease bacteria on the skin

recommended for repeated use

Keep out of reach of children. If swallowed, get medical help or contact a Poison Control Center right away.

INDICATIONS AND USAGE

XtraCare® Instant Hand Sanitizer

Kills 99.9% Of Germs

Moisturizes with Vitamin E

2 FL OZ (60 mL)

Warnings

For external use only.

Flammable, keep away from heat and flame.

Do not use in the eyes. In case of contact, rinse eyes thoroughly with water.

Stop use and ask a doctor if irritation and redness develop and persist for more than 72 hours.

Directions

- wet hands thoroughly with product
- briskly rub hands together until dry
- supervise children under 6 years in the use of this product

Inactive Ingredients

water, carbomer, triethanolamine, glycerin, propylene glycol, fragrance, tocopheryl acetate.

Other Information

- store at 20oC to 25oC (68o to 77oF)
- may discolor certain fabrics

Questions/Comments? 1-855-345-5575

DISTRIBUTED BY

REJOICE INTERNATIONAL INC

NORTHVILLE, MI 48168 USA

MADE IN CHINA